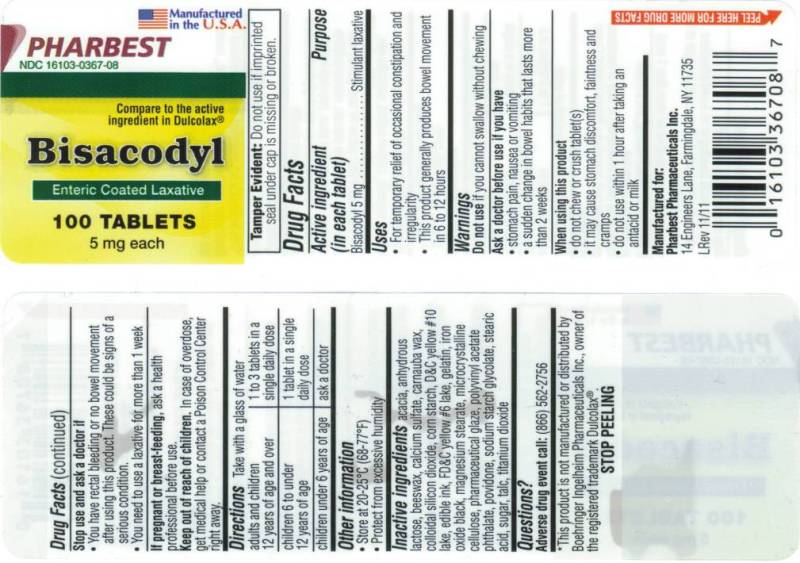 DRUG LABEL: Bisacodyl
NDC: 16103-367 | Form: TABLET, DELAYED RELEASE
Manufacturer: Pharbest Pharmaceuticals Inc.
Category: otc | Type: HUMAN OTC DRUG LABEL
Date: 20120609

ACTIVE INGREDIENTS: BISACODYL  5 mg/1 1
INACTIVE INGREDIENTS: ACACIA; ANHYDROUS LACTOSE; YELLOW WAX; CALCIUM SULFATE; CARNAUBA WAX; SILICON DIOXIDE; STARCH, CORN; D&C YELLOW NO. 10; FD&C YELLOW NO. 6; GELATIN; FERROSOFERRIC OXIDE; MAGNESIUM STEARATE; CELLULOSE, MICROCRYSTALLINE; SHELLAC; POLYVINYL ACETATE PHTHALATE; POVIDONE K30; SODIUM STARCH GLYCOLATE TYPE A POTATO; STEARIC ACID; SUCROSE; TALC; TITANIUM DIOXIDE

Drug facts

Active ingredient (in each tablet)

Bisacodyl 5 mg

PURPOSE

Stimulant laxative

INDICATIONS AND USAGE

- For temporary relief of occasional constipation and irregularity
- This product generally produces bowel movement in 6 to 12 hours

Warnings

Do not use

if you cannot swallow without chewing

Ask a doctor before use if you have

- stomach pain, nausea or vomiting
- a sudden change in bowel habits that lasts more than 2 weeks

When using this product

- do not chew or crush tablet(s)
- it may cause stomach discomfort, faintness and cramps
- do not use within 1 hour after taking an antacid or milk

Stop use and ask a doctor if

- You have rectal bleeding or no bowel movement after using this product. These could be signs of a serious condition.
- You need to use a laxative for more than 1 week

If pregnant or breast-feeding,

ask a health professional before use.

Keep out of reach of children.

In case of overdose, get medical help or contact a Poison Control Center right away.

Directions

Take with a glass of water

adults and children 12 years of age and over | 1 to 3 tablets in a single daily dose
children 6 to under 12 years of age | 1 tablet in a single daily dose
children under 6 years of age | ask a doctor

Other information

- Store at 20 - 25^0C (68-77^0F)
- Protect from excessive humidity

Questions?

Adverse drug event call: (866) 562-2756